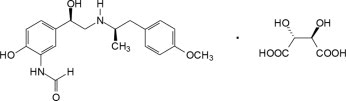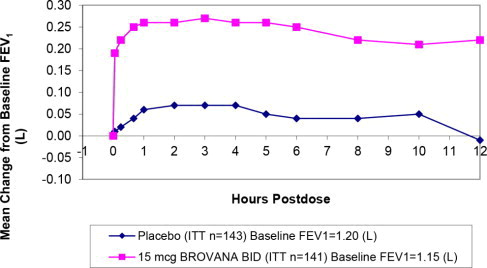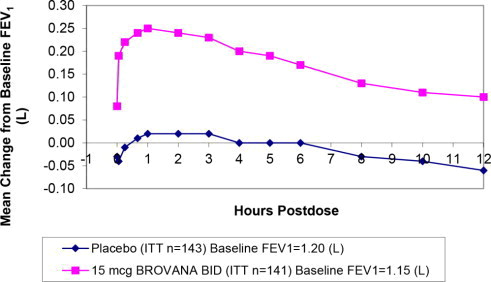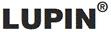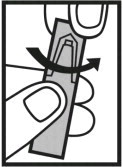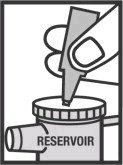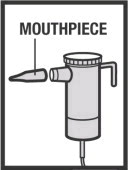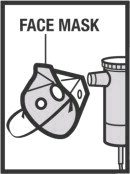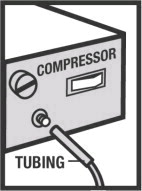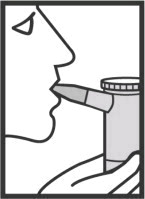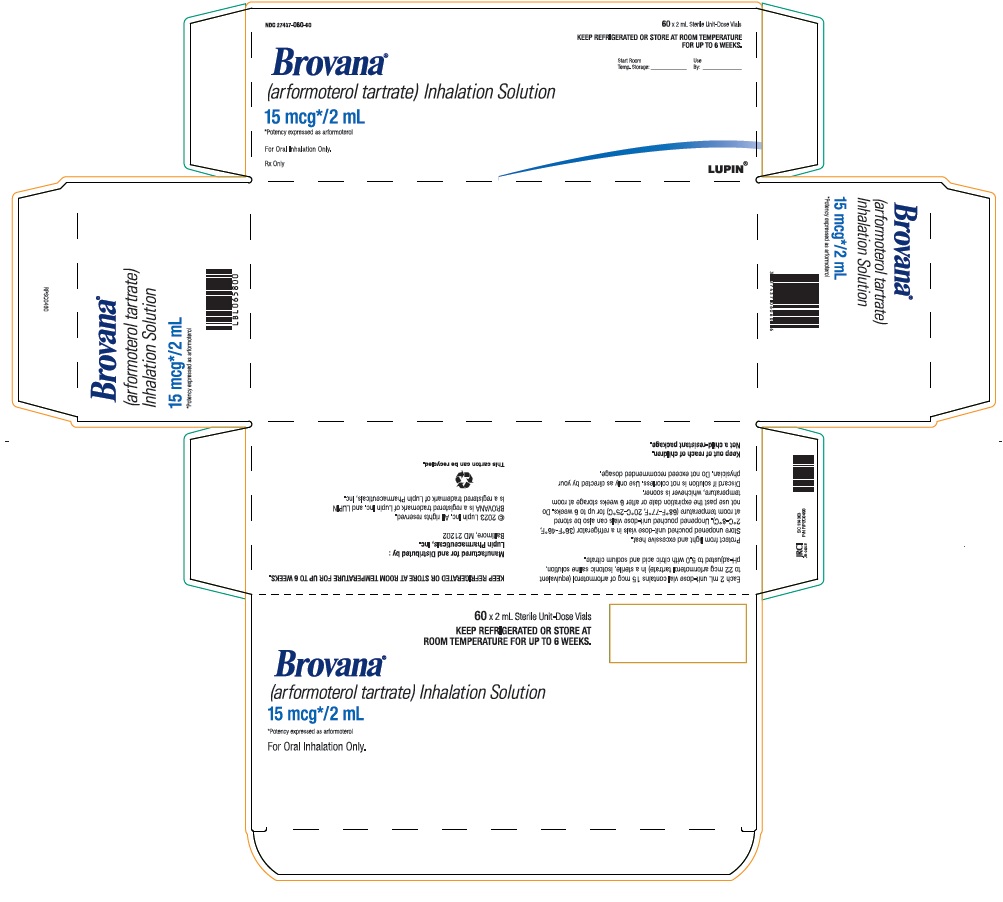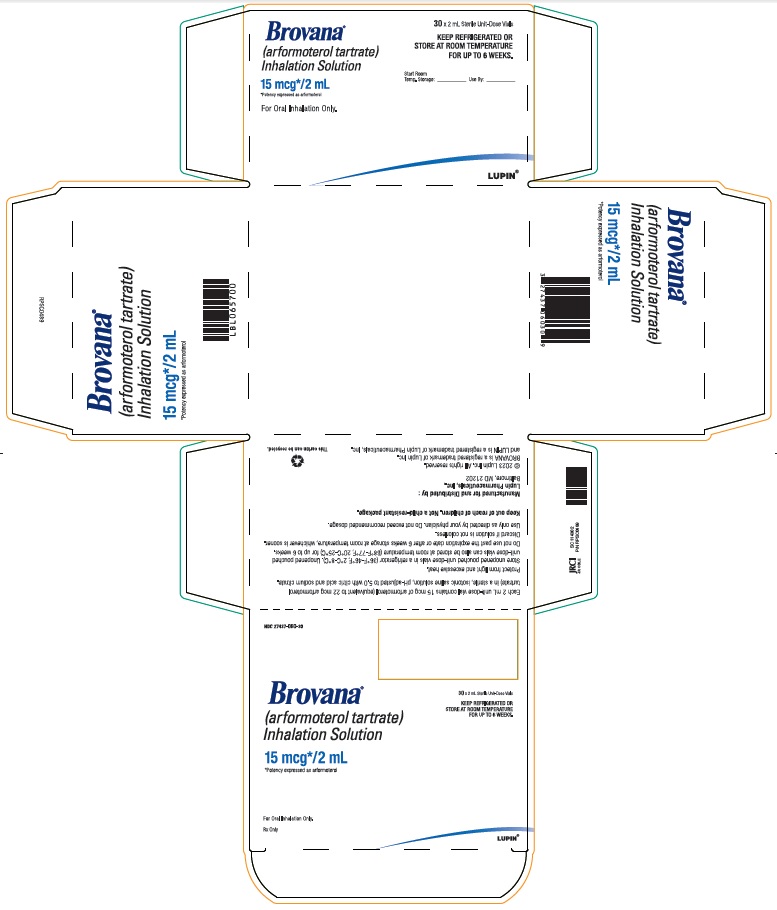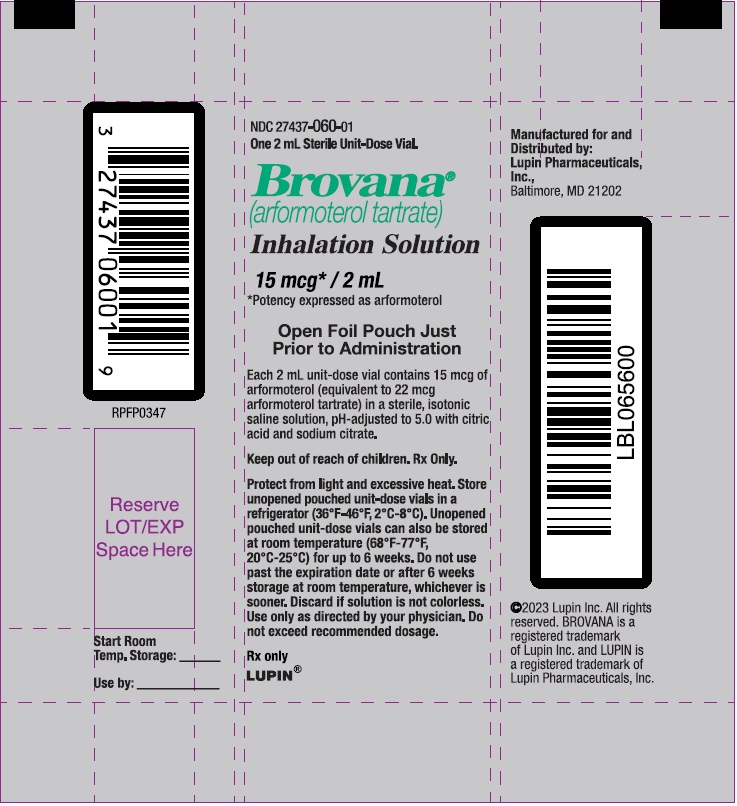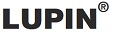 DRUG LABEL: BROVANA
NDC: 27437-060 | Form: SOLUTION
Manufacturer: Lupin Pharmaceuticals, Inc.
Category: prescription | Type: HUMAN PRESCRIPTION DRUG LABEL
Date: 20240415

ACTIVE INGREDIENTS: ARFORMOTEROL TARTRATE 15 ug/2 mL
INACTIVE INGREDIENTS: SODIUM CHLORIDE; TRISODIUM CITRATE DIHYDRATE; WATER; ANHYDROUS CITRIC ACID

HIGHLIGHTS OF PRESCRIBING INFORMATION

These highlights do not include all the information needed to use BROVANA® safely and effectively. See full prescribing information for BROVANA.
BROVANA® (arformoterol tartrate) Inhalation Solution
Initial U.S. Approval: 2006

RECENT MAJOR CHANGES

Box Warning …………………………………….Removed 05/2019

Contraindications, revised (4)………………………………. 05/2019

Warnings and Precautions, revised……………………….….05/2019

Serious Asthma-Related Events – Hospitalizations, Intubations, Death (5.1)

1 INDICATIONS AND USAGE

BROVANA Inhalation Solution is a long-acting beta2-adrenergic agonist (beta2-agonist) indicated for:

- Long-term, twice daily (morning and evening) administration in the maintenance treatment of broncho-constriction in patients with chronic obstructive pulmonary disease (COPD), including chronic bronchitis and emphysema. (1.1)

Important limitations of use:

- BROVANA Inhalation Solution is not indicated to treat acute deteriorations of chronic obstructive pulmonary disease. (1.2, 5.2)
- BROVANA Inhalation Solution is not indicated to treat asthma. (1.2)

2 DOSAGE AND ADMINISTRATION

For oral inhalation only.

- A total daily dose of greater than 30 mcg is not recommended. (2)
- One 15 mcg/2 mL vial every 12 hours. (2)
- For use with a standard jet nebulizer (with a face mask or mouthpiece) connected to an air compressor. (2)

3 DOSAGE FORMS AND STRENGTHS

Inhalation Solution (unit-dose vial for nebulization): 15 mcg/2 mL solution (3)

4 CONTRAINDICATIONS

- BROVANA Inhalation Solution is contraindicated in patients with a history of hypersensitivity to arformoterol, racemic formoterol or to any other components of this product. (4)
- Use of a LABA, including BROVANA Inhalation Solution, without an inhaled corticosteroid is contraindicated in patients with asthma. (4)

5 WARNINGS AND PRECAUTIONS

- LABA as monotherapy (without an inhaled corticosteroid) for asthma increases the risk of serious asthma-related events. (5.1)
- Do not initiate BROVANA Inhalation Solution in acutely deteriorating patients. (5.2)
- Do not use for relief of acute symptoms. Concomitant short-acting beta2-agonists can be used as needed for acute relief. (5.2)
- Do not exceed the recommended dose. Excessive use of BROVANA Inhalation Solution, or use in conjunction with other medications containing long-acting beta2-agonists, can result in clinically significant cardiovascular effects, and may be fatal. (5.3, 5.5)
- Life-threatening paradoxical bronchospasm can occur. Discontinue BROVANA Inhalation Solution immediately. (5.4)
- Use with caution in patients with cardiovascular or convulsive disorders, thyrotoxicosis, or with sensitivity to sympathomimetic drugs. (5.6, 5.7)

6 ADVERSE REACTIONS

Most common adverse reactions (≥2% incidence and more common than placebo) are pain, chest pain, back pain, diarrhea, sinusitis, leg cramps, dyspnea, rash, flu syndrome, peripheral edema and lung disorder. (6.2)

To report SUSPECTED ADVERSE REACTIONS, contact Lupin Pharmaceuticals, Inc. at 1-800-399-2561 or FDA at 1-800-FDA-1088 or www.fda.gov/medwatch.

7 DRUG INTERACTIONS

- Other adrenergic drugs may potentiate effect. Use with caution. (5.3, 7.1)
- Xanthine derivatives, steroids, diuretics, or non-potassium sparing diuretics may potentiate hypokalemia or ECG changes. Use with caution. (5.7, 7.2, 7.3)
- MAO inhibitors, tricyclic antidepressants and drugs that prolong the QTc interval may potentiate effect on the cardiovascular system. Use with extreme caution. (7.4)
- Beta-blockers may decrease effectiveness. May block bronchodilatory effects of beta-agonists. Use with caution and only when medically necessary. (7.5)

8 USE IN SPECIFIC POPULATIONS

- Hepatic Impairment
- Use with caution in patients with hepatic impairment. (8.6)

FULL PRESCRIBING INFORMATION

1 INDICATIONS AND USAGE

1.1 Maintenance Treatment of COPD

BROVANA (arformoterol tartrate) Inhalation Solution is indicated for the long-term, twice daily (morning and evening) maintenance treatment of bronchoconstriction in patients with chronic obstructive pulmonary disease (COPD), including chronic bronchitis and emphysema. BROVANA Inhalation Solution is for use by nebulization only.

1.2 Important Limitations of Use

BROVANA Inhalation Solution is not indicated to treat acute deteriorations of chronic obstructive pulmonary disease [see Warnings and Precautions (5.2)].

BROVANA Inhalation Solution is not indicated to treat asthma. The safety and effectiveness of BROVANA Inhalation Solution in asthma have not been established.

2 DOSAGE AND ADMINISTRATION

The recommended dose of BROVANA (arformoterol tartrate) Inhalation Solution is one 15 mcg unit-dose vial administered twice daily (morning and evening) by nebulization. A total daily dose of greater than 30 mcg (15 mcg twice daily) is not recommended.

BROVANA Inhalation Solution should be administered by the orally inhaled route via a standard jet nebulizer connected to an air compressor (see the accompanying Patient Information). BROVANA Inhalation Solution should not be swallowed. BROVANA Inhalation Solution should be stored refrigerated in foil pouches. After opening the pouch, unused unit-dose vials should be returned to, and stored in, the pouch. An opened unit-dose vial should be used right away.

If the recommended maintenance treatment regimen fails to provide the usual response, medical advice should be sought immediately, as this is often a sign of destabilization of COPD. Under these circumstances, the therapeutic regimen should be reevaluated and additional therapeutic options should be considered.

No dose adjustment is required for patients with renal or hepatic impairment. However, since the clearance of BROVANA Inhalation Solution is prolonged in patients with hepatic impairment, they should be monitored closely.

The drug compatibility (physical and chemical), efficacy, and safety of BROVANA Inhalation Solution when mixed with other drugs in a nebulizer have not been established.

The safety and efficacy of BROVANA Inhalation Solution have been established in clinical trials when administered using the PARI LC® Plus nebulizer (with a face mask or mouthpiece) and the PARI DURA NEB™ 3000 compressor. The safety and efficacy of BROVANA Inhalation Solution delivered from non-compressor based nebulizer systems have not been established.

3 DOSAGE FORMS AND STRENGTHS

BROVANA (arformoterol tartrate) Inhalation Solution is supplied as a sterile solution for nebulization in low-density polyethylene unit-dose vials. Each 2 mL vial contains 15 mcg of arformoterol equivalent to 22 mcg of arformoterol tartrate.

4 CONTRAINDICATIONS

BROVANA Inhalation Solution is contraindicated in patients with a history of hypersensitivity to arformoterol, racemic formoterol or to any other components of this product.

Use of a LABA, including BROVANA Inhalation Solution, without an inhaled cortisteroid is contraindicated in patients with asthma [see Warnings and Precautions (5)]. BROVANA Inhalation Solution is not indicated for the treatment of asthma.

5 WARNINGS AND PRECAUTIONS

5.1 Serious Asthma-Related Events - Hospitalizations, Intubations, Deaths

- The safety and efficacy of BROVANA Inhalation Solution in patients with asthma have not been established. BROVANA Inhalation Solution is not indicated for the treatment of asthma [see Contraindications (4)].
- Use of long-acting beta2-adrenergic agonists (LABA) as monotherapy [without inhaled corticosteroids (ICS)] for asthma is associated with an increased risk of asthma-related death. Available data from controlled clinical trials also suggest that use of LABA as monotherapy increases the risk of asthma-related hospitalization in pediatric and adolescent patients. These findings are considered a class effect of LABA monotherapy. When LABA are used in fixed-dose combination with ICS, data from large clinical trials do not show a significant increase in the risk of serious asthma-related events (hospitalizations, intubations, and death) compared with ICS alone.
- A 28-week, placebo-controlled US study comparing the safety of another LABA (salmeterol) with placebo, each added to usual asthma therapy, showed an increase in asthma-related deaths in patients receiving salmeterol (13/13,176 in patients treated with salmeterol vs. 3/13,179 in patients treated with placebo; RR 4.37, 95% CI 1.25, 15.34). The increased risk of asthma-related death is considered a class effect of the LABA, including BROVANA Inhalation Solution.
- No study adequate to determine whether the rate of asthma-related death is increased in patients treated with BROVANA Inhalation Solution has been conducted. Clinical studies with racemic formoterol suggested a higher incidence of serious asthma exacerbations in patients who received racemic formoterol than in those who received placebo. The sizes of these studies were not adequate to precisely quantify the differences in serious asthma exacerbation rates between treatment groups.
- Available data do not suggest an increased risk of death with use of LABA in patients with COPD.

5.2 Deterioration of Disease and Acute Episodes

BROVANA Inhalation Solution should not be initiated in patients with acutely deteriorating COPD, which may be a life-threatening condition. The use of BROVANA Inhalation Solution in this setting is inappropriate.

BROVANA Inhalation Solution is not indicated for the treatment of acute episodes of bronchospasm, i.e., as rescue therapy and extra doses should not be used for that purpose. Acute symptoms should be treated with an inhaled short-acting beta2-agonist.

When beginning BROVANA Inhalation Solution, patients who have been taking inhaled short-acting beta2-agonists on a regular basis (e.g., four times a day) should be instructed to discontinue the regular use of these drugs and use them only for symptomatic relief of acute respiratory symptoms. When prescribing BROVANA Inhalation Solution, the healthcare provider should also prescribe an inhaled, short-acting beta2-agonist and instruct the patient how it should be used. Increasing inhaled beta2-agonist use is a signal of deteriorating disease for which prompt medical attention is indicated. COPD may deteriorate acutely over a period of hours or chronically over several days or longer. If BROVANA Inhalation Solution no longer controls the symptoms of bronchoconstriction, or the patient's inhaled, short-acting beta2-agonist becomes less effective or the patient needs more inhalation of short-acting beta2-agonist than usual, these may be markers of deterioration of disease. In this setting, a reevaluation of the patient and the COPD treatment regimen should be undertaken at once. Increasing the daily dosage of BROVANA Inhalation Solution beyond the recommended 15 mcg twice daily dose is not appropriate in this situation.

5.3 Excessive Use of BROVANA Inhalation Solution and Use with Other Long-Acting Beta2-Agonists

Fatalities have been reported in association with excessive use of inhaled sympathomimetic drugs. As with other inhaled beta2-adrenergic drugs, BROVANA Inhalation Solution should not be used more often, at higher doses than recommended, or in conjunction with other medications containing long-acting beta2-agonists.

5.4 Paradoxical Bronchospasm

As with other inhaled beta2-agonists, BROVANA Inhalation Solution can produce paradoxical bronchospasm that may be life-threatening. If paradoxical bronchospasm occurs, BROVANA Inhalation Solution should be discontinued immediately and alternative therapy instituted.

5.5 Cardiovascular Effects

BROVANA Inhalation Solution, like other beta2-agonists, can produce a clinically significant cardiovascular effect in some patients as measured by increases in pulse rate, systolic and/or diastolic blood pressure, and/or symptoms. If such effects occur, the drug may need to be discontinued. In addition, beta-agonists have been reported to produce ECG changes, such as flattening of the T-wave, prolongation of the QTc interval, and ST segment depression. The clinical significance of these findings is unknown. BROVANA Inhalation Solution, as with other sympathomimetic amines, should be used with caution in patients with cardiovascular disorders, especially coronary insufficiency, cardiac arrhythmias, and hypertension.

5.6 Coexisting Conditions

BROVANA Inhalation Solution, like other sympathomimetic amines, should be used with caution in patients with cardiovascular disorders, especially coronary insufficiency, cardiac arrhythmias, and hypertension; in patients with convulsive disorders or thyrotoxicosis, and in patients who are unusually responsive to sympathomimetic amines. In two pooled, 12-week, placebo-controlled trials investigating BROVANA Inhalation Solution doses of 15 μg BID, 25 μg BID, and 50 μg QD, changes in mean predose and 2-hour post dose systolic and/or diastolic blood pressure were seen as a general fall of 2-4 mm/Hg; for pulse rate the mean of maximal increases were 8.8-12.0 beats/min. Over the course of a one-year study measuring serial electrocardiograms while receiving a dose of 50 mcg daily of BROVANA Inhalation Solution resulted in an approximately 3.0 ms increase in QTC-F compared to the active comparator, salmeterol. Doses of the related beta2-agonist albuterol, when administered intravenously, have been reported to aggravate preexisting diabetes mellitus and ketoacidosis.

5.7 Hypokalemia and Hyperglycemia

Beta-agonist medications may produce significant hypokalemia in some patients, possibly through intracellular shunting, which has the potential to produce adverse cardiovascular effects [see Clinical Pharmacology (12.2)]. The decrease in serum potassium is usually transient, not requiring supplementation. Beta-agonist medications may produce transient hyperglycemia in some patients.

Clinically significant and dose-related changes in serum potassium and blood glucose were infrequent during clinical trials with long-term administration of BROVANA Inhalation Solution at the recommended dose.

5.8 Immediate Hypersensitivity Reactions

Immediate hypersensitivity reactions may occur after administration of BROVANA Inhalation Solution as demonstrated by cases of anaphylactic reaction, urticaria, angioedema, rash and bronchospasm.

6 ADVERSE REACTIONS

Long-acting beta2-adrenergic agonists, such as BROVANA, as monotherapy (without inhaled corticosteroids) for asthma increase the risk of asthma-related events. BROVANA Inhalation Solution is not indicated for the treatment of asthma [see Warnings and Precautions (5.1)].

6.1 Beta2-Agonist Adverse Reaction Profile

Adverse reactions to BROVANA Inhalation Solution are expected to be similar in nature to other beta2-adrenergic receptor agonists including: angina, hypertension or hypotension, tachycardia, arrhythmias, nervousness, headache, tremor, dry mouth, palpitation, muscle cramps, nausea, dizziness, fatigue, malaise, hypokalemia, hyperglycemia, metabolic acidosis and insomnia.

6.2 Clinical Trials Experience

Because clinical trials are conducted under widely varying conditions, adverse reaction rates observed in clinical trials of a drug cannot be directly compared to rates in the clinical trials of another drug and may not reflect the rates observed in clinical practice.

Adults with COPD in Short-Term Trials (12 weeks)

The safety data described below for adults ≥35 years of age are based on 2 clinical trials of 12 weeks. In the 2 trials of 12 weeks duration, 1456 patients (860 males and 596 females, ages 34 to 89 years old) with COPD were treated with BROVANA Inhalation Solution 15 mcg twice daily, 25 mcg twice daily, 50 mcg once daily, salmeterol 42 mcg twice daily, or placebo. The racial/ethnic distribution in these two trials included 1383 Caucasians, 49 Blacks, 10 Asians, and 10 Hispanics, and 4 patients classified as Other.

Among the 1,456 COPD patients in two 12-week, placebo-controlled trials, 288 were treated with BROVANA Inhalation Solution 15 mcg twice daily and 293 were treated with placebo. Doses of 25 mcg twice daily and 50 mcg once daily were also evaluated.

Table 1 shows adverse reaction rates among patients from these two trials where the frequency was greater than or equal to 2% in the BROVANA Inhalation Solution 15 mcg twice daily group and where the rate in the BROVANA Inhalation Solution 15 mcg twice daily group exceeded the rate in the placebo group. The total number and percent of patients who reported adverse events were 202 (70%) in the 15 mcg twice daily and 219 (75%) in the placebo groups. Ten adverse events demonstrated a dose relationship: asthenia, fever, bronchitis, COPD, headache, vomiting, hyperkalemia, leukocytosis, nervousness, and tremor.

Table 1: Number of Patients Experiencing Adverse Events from Two 12-Week, Double-Blind, Placebo-Controlled Clinical Trials
 | BROVANA Inhalation Solution 15 mcg twice daily |  | Placebo
 | n | (%) | n | (%)
Total Patients | 288 | (100) | 293 | (100)
Pain | 23 | (8) | 16 | (5)
Chest Pain | 19 | (7) | 19 | (6)
Back Pain | 16 | (6) | 6 | (2)
Diarrhea | 16 | (6) | 13 | (4)
Sinusitis | 13 | (5) | 11 | (4)
Leg Cramps | 12 | (4) | 6 | (2)
Dyspnea | 11 | (4) | 7 | (2)
Rash | 11 | (4) | 5 | (2)
Flu Syndrome | 10 | (3) | 4 | (1)
Peripheral Edema | 8 | (3) | 7 | (2)
Lung Disorder [Reported terms coded to "Lung Disorder" were predominantly pulmonary or chest congestion.] | 7 | (2) | 2 | (1)

Adverse events occurring in patients treated with BROVANA Inhalation Solution 15 mcg twice daily with a frequency of <2%, but greater than placebo, were as follows:

Body as a Whole: abscess, allergic reaction, digitalis intoxication, fever, hernia, injection site pain, neck rigidity, neoplasm, pelvic pain, retroperitoneal hemorrhage

Cardiovascular: arteriosclerosis, atrial flutter, AV block, congestive heart failure, heart block, myocardial infarct, QT interval prolonged, supraventricular tachycardia, inverted T-wave

Digestive: constipation, gastritis, melena, oral moniliasis, periodontal abscess, rectal hemorrhage

Metabolic and Nutritional Disorders: dehydration, edema, glucose tolerance decreased, gout, hyperglycemia, hyperlipemia, hypoglycemia, hypokalemia

Musculoskeletal: arthralgia, arthritis, bone disorder, rheumatoid arthritis, tendinous contracture

Nervous: agitation, cerebral infarct, circumoral paresthesia, hypokinesia, paralysis, somnolence, tremor

Respiratory: carcinoma of the lung, respiratory disorder, voice alteration

Skin and Appendages: dry skin, herpes simplex, herpes zoster, skin discoloration, skin hypertrophy

Special Senses: abnormal vision, glaucoma

Urogenital: breast neoplasm, calcium crystalluria, cystitis, glycosuria, hematuria, kidney calculus, nocturia, PSA increase, pyuria, urinary tract disorder, urine abnormality.

In these trials, the overall frequency of all cardiovascular adverse events was 6.9% in BROVANA Inhalation Solution 15 mcg twice daily and 13.3% in the placebo group. There were no frequently occurring specific cardiovascular adverse events for BROVANA Inhalation Solution (frequency ≥1% and greater than placebo). The rate of COPD exacerbations was also comparable between the BROVANA Inhalation Solution 15 mcg twice daily and placebo groups, 12.2% and 15.1%, respectively.

Adults with COPD in Long-Term (52-week) Safety Trial

BROVANA Inhalation Solution was evaluated in one 52 week double-blind, randomized, placebo-controlled, safety trial conducted in patients with moderate to severe COPD. The primary endpoint was time to either respiratory death or first COPD exacerbation-related hospitalization, whichever occurred first. The event had to be a death or hospitalization for which the patient's respiratory status was predominant and/or inciting contributor, as determined by the clinical investigator. The objective of the trial was to demonstrate that the risk of respiratory death or COPD exacerbation-related hospitalization for patients treated with BROVANA Inhalation Solution was not greater than 40% more than the risk for patient treated with placebo. A total of 841 patients (479 males and 361 females, ages 41 to 94 years old) with COPD were randomized: 420 to BROVANA Inhalation Solution 15 mcg twice daily and 421 to placebo. Of the randomized patients, 255 (61%) in the BROVANA Inhalation Solution group and 211 (50%) in the placebo group, completed one year of treatment. The trial objective was met demonstrating that COPD patients treated with BROVANA Inhalation Solution are not at an increased risk of respiratory death or COPD exacerbation-related hospitalizations compared to placebo.

7 DRUG INTERACTIONS

7.1 Adrenergic Drugs

If additional adrenergic drugs are to be administered by any route, they should be used with caution because the sympathetic effects of arformoterol may be potentiated [see Warnings and Precautions (5.3, 5.5, 5.6, 5.7)].

7.2 Xanthine Derivatives, Steroids, or Diuretics

Concomitant treatment with methylxanthine (aminophylline, theophylline), steroids, or diuretics may potentiate any hypokalemic effect of adrenergic agonists including BROVANA Inhalation Solution [see Warnings and Precautions (5.7)].

The concurrent use of intravenously or orally administered methylxanthines (e.g., aminophylline, theophylline) by patients receiving BROVANA Inhalation Solution has not been completely evaluated. In two combined 12-week, placebo-controlled trials that included BROVANA Inhalation Solution doses of 15 mcg twice daily, 25 mcg twice daily, and 50 mcg once daily, 54 of 873 BROVANA Inhalation Solution-treated subjects received concomitant theophylline at study entry. In a 12-month controlled trial that included a 50 mcg once daily BROVANA Inhalation Solution dose, 30 of the 528 BROVANA Inhalation Solution-treated subjects received concomitant theophylline at study entry. In these trials, heart rate and systolic blood pressure were approximately 2-3 bpm and 6-8 mm Hg higher, respectively, in subjects on concomitant theophylline compared with the overall population.

7.3 Non-potassium Sparing Diuretics

The ECG changes and/or hypokalemia that may result from the administration of non-potassium sparing diuretics (such as loop or thiazide diuretics) can be acutely worsened by beta-agonists, especially when the recommended dose of the beta-agonist is exceeded. Although the clinical significance of these effects is not known, caution is advised in the co-administration of beta-agonists, including BROVANA Inhalation Solution, with non-potassium sparing diuretics.

7.4 MAO Inhibitors, Tricyclic Antidepressants, QTc Prolonging Drugs

BROVANA Inhalation Solution, as with other beta-agonists, should be administered with extreme caution to patients being treated with monoamine oxidase inhibitors, tricyclic antidepressants, or drugs known to prolong the QTc interval because of the effect of adrenergic agonists on the cardiovascular system may be potentiated by these agents. Drugs that are known to prolong the QTc interval have an increased risk of ventricular arrhythmias.

7.5 Beta-Blockers

Beta-adrenergic receptor antagonists (beta-blockers) and BROVANA Inhalation Solution may inhibit the effect of each other when administered concurrently. Beta-blockers not only block the therapeutic effects of beta-agonists, but may produce severe bronchospasm in COPD patients. Therefore, patients with COPD should not normally be treated with beta-blockers. However, under certain circumstances, e.g., as prophylaxis after myocardial infarction, there may be no acceptable alternatives to the use of beta-blockers in patients with COPD. In this setting, cardioselective beta-blockers could be considered, although they should be administered with caution.

8 USE IN SPECIFIC POPULATIONS

8.1 Pregnancy

Risk Summary

There are no adequate and well-controlled studies in pregnant women. BROVANA should only be used during pregnancy if the expected benefit to the patient outweighs the potential risk to the fetus. Women should be advised to contact their physician if they become pregnant while taking BROVANA. In animal reproduction studies with arformoterol administered by the oral route to rats and rabbits at exposures approximately 370 and 8,400 times the adult exposure at the maximum recommended human daily inhalation dose (MRHDID) of 15 mcg every 12 hours, respectively, there were findings of structural abnormalities, embryofetal and infant mortality, and alterations of growth. These adverse effects generally occurred at large multiples of the MRHDID when arformoterol was administered by the oral route to achieve high systemic exposures. No evidence of fetal harm was observed in rabbits at an exposure approximately 4,900 times the MRHDID.

The estimated background risk of major birth defects and miscarriage for the indicated population is unknown. In the U.S. general population, the estimated background risk of major birth defects and miscarriage in clinically recognized pregnancies is 2-4% and 15-20%, respectively.

Clinical Considerations

Labor or Delivery:

The potential effect of BROVANA on labor and delivery is unknown. Because of the potential for beta-agonists interference with uterine contractility, use of BROVANA Inhalation Solution during labor should be restricted to whom the benefits clearly outweigh the risk.

Data

Animal Data

In an embryofetal development study in which pregnant rats received doses of 1,000, 5,000 or 10,000 mcg/kg/day from gestation days 6 to 17, arformoterol was shown to be teratogenic based upon findings of omphalocele (umbilical hernia), a malformation, in rat fetuses at exposures approximately 370 times adult exposure at the MRHDID (on an AUC basis with maternal oral doses of 1,000 mcg/kg/day and higher. Maternal toxicity was not observed in rats with exposures up to 2,400 times the MRHDID (on an AUC basis with maternal oral doses up to 10,000 mcg/kg/day). A no-observed-adverse-effect-level (NOAEL) for rat fetuses was not identified.

In an embryofetal development study in which pregnant rabbits received doses of 20,000, 40,000 or 80,000 mcg/kg/day from gestation days 7 to 20, arformoterol was shown to be teratogenic based upon findings of malpositioned right kidney, a malformation, in rabbit fetuses at exposures approximately 8400 times and higher than the adult exposure at the MRHDID (on an AUC basis with maternal oral doses of 20,000 mcg/kg/day and higher). Malformations including brachydactyly, bulbous aorta, and liver cysts as well as decreased body weights were observed in rabbit fetuses at doses approximately 26,000 times and higher than the MRHDID in adults (on a mcg/m^2 basis with maternal oral doses of 40,000 mcg/kg/day and higher). Malformations including adactyly, lobular dysgenesis of the lung, and interventricular septal defect as well as embryolethality were observed in rabbit fetuses at a dose approximately 52,000 times the MRHDID in adults (on a mcg/m^2 basis with a maternal oral dose of 80,000 mcg/kg/day). Maternal toxicity was observed at doses approximately 26,000 times and higher than the MRHDID in adults (on a mcg/m2 basis with maternal oral doses of 40,000 mcg/kg/day and higher). There was no evidence of fetal harm in rabbits at exposures approximately 4,900 times and lower than the adult exposure at the MRHDID (on an AUC basis with maternal oral doses of 10,000 mcg/kg/day and lower).

In a pre- and post-natal development study, female rats received arformoterol at oral doses of 0, 1,000, 5,000, and 10,000 mcg/kg/day from gestation day 6 through lactation day 20. Lengths of gestation for female rats receiving doses 325 times and higher than the MRHDID (on a mcg/m^2 basis with maternal oral doses of 1,000 mcg/kg/day and higher) were slightly prolonged, which was attributed to prolonged parturition or dystocia due to the pharmacological action of β-adrenergic agonists such as arformoterol to relax uterine musculature. One female that had received a dose 3,200 times the MRHDID (on a mcg/m^2 basis with a maternal oral dose of 10,000 mcg/kg/day) was euthanized due to complications during parturition. Pup survival and body weights were decreased at doses 1,600 times and higher than the MRHDID (on a mcg/m^2 basis with maternal oral doses of 5,000 mcg/kg/day and higher) at birth and during lactation. Umbilical hernia, a malformation, was observed for 1 pup at a dose 3,200 times the MRHDID (on a mcg/m^2 basis with a maternal oral dose of 10,000 mcg/kg/day). Potential developmental delays of rat pups were observed at a dose 3,200 times the MRHDID (on a mcg/m^2 basis with a maternal oral dose of 10,000 mcg/kg/day); however, no developmental delays were evident with doses 1,600 times the MRHDID (on a mcg/m^2 basis with a maternal oral dose of 5,000 mcg/kg/day).

8.2 Lactation

Risk Summary

There are no data on the presence of arformoterol or its metabolites in human milk, the effects on the breastfed infant, or the effects on milk production. However, arformoterol was excreted in the milk of lactating rats. The developmental and health benefits of breastfeeding should be considered along with the mother's clinical need for BROVANA and any potential adverse effects on the breastfed infant from BROVANA or from the underlying maternal condition.

Data

Arformoterol and its metabolites were detected in the milk of lactating rats following oral administration of a 10,000 mcg/kg dose of radiolabeled arformoterol tartrate.

8.4 Pediatric Use

BROVANA Inhalation Solution is approved for use in the long-term maintenance treatment of broncho-constriction associated with chronic obstructive pulmonary disease, including chronic bronchitis and emphysema. This disease does not occur in children. The safety and efficacy of BROVANA Inhalation Solution in pediatric patients have not been established.

8.5 Geriatric Use

Of the 873 patients who received BROVANA Inhalation Solution in two placebo-controlled clinical studies in adults with COPD, 391 (45%) were 65 years of age or older while 96 (11%) were 75 years of age or older. No overall differences in safety or effectiveness were observed between these subjects and younger subjects. Among subjects age 65 years and older, 129 (33%) received BROVANA Inhalation Solution at the recommended dose of 15 mcg twice daily, while the remainder received higher doses. ECG alerts for ventricular ectopy in patients 65 to ≤75 years of age were comparable among patients receiving 15 mcg twice daily, 25 mcg twice daily, and placebo (3.9%, 5.2%, and 7.1%, respectively). A higher frequency (12.4%) was observed when BROVANA Inhalation Solution was dosed at 50 mcg once daily. The clinical significance of this finding is not known. Other reported clinical experience has not identified differences in responses between the elderly and younger patients, but greater sensitivity of some older individuals cannot be ruled out.

8.6 Hepatic Impairment

BROVANA Inhalation Solution should be used cautiously in patients with hepatic impairment due to increased systemic exposure in these patients [see Clinical Pharmacology (12.3)].

8.7 Renal Impairment

The systemic exposure to arformoterol was similar to renally impaired patients compared with demographically matched healthy control subjects [see Clinical Pharmacology (12.3)].

9 DRUG ABUSE AND DEPENDENCE

There were no reported cases of abuse or evidence of drug dependence with the use of BROVANA Inhalation Solution in the clinical trials.

10 OVERDOSAGE

The expected signs and symptoms associated with overdosage of BROVANA (arformoterol tartrate) Inhalation Solution are those of excessive beta-adrenergic stimulation and/or occurrence or exaggeration of any of the signs and symptoms listed under ADVERSE REACTIONS. Signs and symptoms may include angina, hypertension or hypotension, tachycardia, with rates up to 200 beats/min, arrhythmias, nervousness, headache, tremor, dry mouth, palpitation, muscle cramps, nausea, dizziness, fatigue, malaise, hypokalemia, hyperglycemia, metabolic acidosis and insomnia. As with all inhaled sympathomimetic medications, cardiac arrest and even death may be associated with an overdose of BROVANA Inhalation Solution.

Treatment of overdosage consists of discontinuation of BROVANA Inhalation Solution together with institution of appropriate symptomatic and/or supportive therapy. The judicious use of a cardioselective beta-receptor blocker may be considered, bearing in mind that such medication can produce bronchospasm. There is insufficient evidence to determine if dialysis is beneficial for overdosage of BROVANA Inhalation Solution. Cardiac monitoring is recommended in cases of overdosage.

11 DESCRIPTION

BROVANA (arformoterol tartrate) Inhalation Solution is a sterile, clear, colorless, aqueous solution of the tartrate salt of arformoterol, the (R,R)-enantiomer of formoterol.

Arformoterol is a selective beta2-adrenergic bronchodilator. The chemical name for arformoterol tartrate is formamide, N-[2-hydroxy-5-[(1R)-1-hydroxy-2-[[(1R)-2-(4-methoxyphenyl)-1-methylethyl]amino]ethyl]phenyl]-, (2R,3R)-2,3-dihydroxybutanedioate (1:1 salt), and its established structural formula is as follows:

The molecular weight of arformoterol tartrate is 494.5 g/mol, and its empirical formula is C19H24N2O4•C4H6O6 (1:1 salt). It is a white to off-white solid that is slightly soluble in water.

Arformoterol tartrate is the United States Adopted Name (USAN) for (R,R)-formoterol L-tartrate.

BROVANA (arformoterol tartrate) Inhalation Solution is supplied as 2 mL of arformoterol tartrate solution packaged in 2.1 mL unit-dose, low-density polyethylene (LDPE) unit-dose vials. Each unit-dose vial contains 15 mcg of arformoterol (equivalent to 22 mcg of arformoterol tartrate) in a sterile, isotonic saline solution, pH-adjusted to 5.0 with citric acid and sodium citrate.

BROVANA Inhalation Solution requires no dilution before administration by nebulization. Like all other nebulized treatments, the amount delivered to the lungs will depend upon patient factors, the nebulizer used, and compressor performance. Using the PARI LC® Plus nebulizer (with mouthpiece) connected to a PARI DURA NEB™ 3000 compressor under in vitro conditions, the mean delivered dose from the mouthpiece (% nominal) was approximately 4.1 mcg (27.6%) at a mean flow rate of 3.3 L/min. The mean nebulization time was 6 minutes or less. BROVANA Inhalation Solution should be administered from a standard jet nebulizer at adequate flow rates via face mask or mouthpiece.

Patients should be carefully instructed on the correct use of this drug product (please refer to the accompanying Patient Information).

12 CLINICAL PHARMACOLOGY

12.1 Mechanism of Action

Arformoterol, the (R,R)-enantiomer of formoterol, is a selective long-acting beta2-adrenergic receptor agonist (beta2-agonist) that has two-fold greater potency than racemic formoterol (which contains both the (S,S) and (R,R)-enantiomers). The (S,S)-enantiomer is about 1,000-fold less potent as a beta2-agonist than the (R,R)-enantiomer. While it is recognized that beta2-receptors are the predominant adrenergic receptors in bronchial smooth muscle and beta1-receptors are the predominant receptors in the heart, data indicate that there are also beta2-receptors in the human heart comprising 10% to 50% of the total beta-adrenergic receptors. The precise function of these receptors has not been established, but they raise the possibility that even highly selective beta2-agonists may have cardiac effects.

The pharmacologic effects of beta2-adrenoceptor agonist drugs, including arformoterol, are at least in part attributable to stimulation of intracellular adenyl cyclase, the enzyme that catalyzes the conversion of adenosine triphosphate (ATP) to cyclic-3′,5′-adenosine monophosphate (cyclic AMP). Increased intracellular cyclic AMP levels cause relaxation of bronchial smooth muscle and inhibition of release of mediators of immediate hypersensitivity from cells, especially from mast cells.

In vitro tests show that arformoterol is an inhibitor of the release of mast cell mediators, such as histamine and leukotrienes, from the human lung. Arformoterol also inhibits histamine-induced plasma albumin extravasation in anesthetized guinea pigs and inhibits allergen-induced eosinophil influx in dogs with airway hyper-responsiveness. The relevance of these in vitro and animal findings to humans is unknown.

12.2 Pharmacodynamics

Systemic Safety and Pharmacokinetic/Pharmacodynamic Relationships

The predominant adverse effects of inhaled beta2-agonists occur as a result of excessive activation of systemic beta-adrenergic receptors. The most common adverse effects may include skeletal muscle tremor and cramps, insomnia, tachycardia, decreases in plasma potassium, and increases in plasma glucose.

Effects on Serum Potassium and Serum Glucose Levels

Changes in serum potassium and serum glucose were evaluated in a dose-ranging study of twice daily (5 mcg, 15 mcg, or 25 mcg; 215 patients with COPD) and once daily (15 mcg, 25 mcg, or 50 mcg; 191 patients with COPD) BROVANA Inhalation Solution in COPD patients. At 2 and 6 hours post dose at week 0 (after the first dose), mean changes in serum potassium ranging from 0 to -0.3 mEq/L were observed in the BROVANA Inhalation Solution groups with similar changes observed after 2 weeks of treatment. Changes in mean serum glucose levels, ranging from a decrease of 1.2 mg/dL to an increase of 32.8 mg/dL were observed for BROVANA Inhalation Solution dose groups at both 2 and 6 hours post dose, both after the first dose and 14 days of daily treatment.

Electrophysiology

The effect of BROVANA Inhalation Solution on QT interval was evaluated in a dose-ranging study following multiple doses of BROVANA Inhalation Solution 5 mcg, 15 mcg, or 25 mcg twice daily or 15 mcg, 25 mcg, or 50 mcg once daily for 2 weeks in patients with COPD. ECG assessments were performed at baseline, time of peak plasma concentration and throughout the dosing interval. Different methods of correcting for heart rate were employed, including a subject-specific method and the Fridericia method.

Relative to placebo, the mean change in subject-specific QTc averaged over the dosing interval ranged from -1.8 to 2.7 msec, indicating little effect of BROVANA Inhalation Solution on cardiac repolarization after 2 weeks of treatment. The maximum mean change in subject-specific QTc for the BROVANA Inhalation Solution 15 mcg twice daily dose was 17.3 msec, compared with 15.4 msec in the placebo group. No apparent correlation of QTc with arformoterol plasma concentration was observed.

Electrocardiographic Monitoring in Patients with COPD

The effect of different doses of BROVANA Inhalation Solution on cardiac rhythm was assessed using 24-hour Holter monitoring in two 12-week, double-blind, placebo-controlled studies of 1,456 patients with COPD (873 received BROVANA Inhalation Solution at 15 or 25 mcg twice daily or 50 mcg once daily doses; 293 received placebo; 290 received salmeterol). The 24-hour Holter monitoring occurred once at baseline, and up to 3 times during the 12-week treatment period. The rates of new-onset cardiac arrhythmias not present at baseline over the double-blind 12-week treatment period were similar (approximately 33-34%) for patients who received BROVANA Inhalation Solution 15 mcg twice daily to those who received placebo. There was a dose-related increase in new, treatment-emergent arrhythmias seen in patients who received BROVANA Inhalation Solution 25 mcg twice daily and 50 mcg once daily, 37.6% and 40.1%, respectively. The frequencies of new treatment-emergent events of non-sustained (3-10 beat run) and sustained (>10 beat run) ventricular tachycardia were 7.4% and 1.1% in BROVANA Inhalation Solution 15 mcg twice daily and 6.9% and 1.0% in placebo. In patients who received BROVANA Inhalation Solution 25 mcg twice daily and 50 mcg once daily, the frequencies of non-sustained (6.2% and 8.2%, respectively) and sustained ventricular tachycardia (1.0% and 1.0%, respectively) were similar. Five cases of ventricular tachycardia were reported as adverse events (1 in BROVANA Inhalation Solution 15 mcg twice daily and 4 in placebo), with two of these events leading to discontinuation of treatment (2 in placebo).

There were no baseline occurrences of atrial fibrillation/flutter observed on 24-hour Holter monitoring in patients treated with BROVANA Inhalation Solution 15 mcg twice daily or placebo. New, treatment-emergent atrial fibrillation/flutter occurred in 0.4% of patients who received BROVANA Inhalation Solution 15 mcg twice daily and 0.3% of patients who received placebo. There was a dose-related increase in the frequency of atrial fibrillation/flutter reported in the BROVANA Inhalation Solution 25 mcg twice daily and 50 mcg once daily dose groups of 0.7% and 1.4%, respectively. Two cases of atrial fibrillation/flutter were reported as adverse events (1 in BROVANA Inhalation Solution 15 mcg twice daily and 1 in placebo).

Dose-related increases in mean maximum change in heart rate in the 12 hours after dosing were also observed following 12 weeks of dosing with BROVANA Inhalation Solution 15 mcg twice daily (8.8 bpm), 25 mcg twice daily (9.9 bpm) and 50 mcg once daily (12 bpm) versus placebo (8.5 bpm).

Tachyphylaxis/Tolerance

Tolerance to the effects of inhaled beta-agonists can occur with regularly-scheduled, chronic use.

In two placebo-controlled clinical trials in patients with COPD involving approximately 725 patients in each, the overall efficacy of BROVANA Inhalation Solution was maintained throughout the 12-week trial duration. However, tolerance to the bronchodilator effect of BROVANA Inhalation Solution was observed after 6 weeks of dosing, as measured by a decrease in trough FEV1. FEV1 improvement at the end of the 12-hour dosing interval decreased by approximately one-third (22.1% mean improvement after the first dose compared to 14.6% at week 12). Tolerance to the trough FEV1 bronchodilator effect of BROVANA Inhalation Solution was not accompanied by other clinical manifestations of tolerance in these trials.

12.3 Pharmacokinetics

The pharmacokinetics (PK) of arformoterol have been investigated in healthy subjects, elderly subjects, renally and hepatically impaired subjects, and COPD patients following the nebulization of the recommended therapeutic dose and doses up to 96 mcg.

Absorption

In COPD patients administered 15 mcg arformoterol every 12 hours for 14 days, the mean steady-state peak (R,R)-formoterol plasma concentration (Cmax) and systemic exposure (AUC0-12h) were 4.3 pg/mL and 34.5 pg•hr/mL, respectively. The median steady-state peak (R,R)-formoterol plasma concentration time (tmax) was observed approximately one-half hour after drug administration.

Systemic exposure to (R,R)-formoterol increased linearly with dose in COPD patients following arformoterol doses of 5 mcg, 15 mcg, or 25 mcg twice daily for 2 weeks or 15 mcg, 25 mcg, or 50 mcg once daily for 2 weeks.

In a crossover study in patients with COPD, when arformoterol 15 mcg inhalation solution and 12 and 24 mcg formoterol fumarate inhalation powder (Foradil® Aerolizer®) was administered twice daily for 2 weeks, the accumulation index was approximately 2.5 based on the plasma (R,R)-formoterol concentrations in all three treatments. At steady- state, geometric means of systemic exposure (AUC0-12h) to (R,R)-formoterol following 15 mcg of arformoterol inhalation solution and 12 mcg of formoterol fumarate inhalation powder were 39.33 pg•hr/mL and 33.93 pg•hr/mL, respectively (ratio 1.16; 90% CI 1.00, 1.35), while the geometric means of the Cmax were 4.30 pg/mL and 4.75 pg/mL, respectively (ratio 0.91; 90% CI 0.76, 1.09).

In a study in patients with asthma, treatment with arformoterol 50 mcg with pre- and post-treatment with activated charcoal resulted in a geometric mean decrease in (R,R)-formoterol AUC0-6h by 27% and Cmax by 23% as compared to treatment with arformoterol 50 mcg alone. This suggests that a substantial portion of systemic drug exposure is due to pulmonary absorption.

Distribution

The binding of arformoterol to human plasma proteins in vitro was 52-65% at concentrations of 0.25, 0.5 and 1.0 ng/mL of radiolabeled arformoterol. The concentrations of arformoterol used to assess the plasma protein binding were higher than those achieved in plasma following inhalation of multiple doses of 50 mcg arformoterol.

Metabolism

In vitro profiling studies in hepatocytes and liver microsomes have shown that arformoterol is primarily metabolized by direct conjugation (glucuronidation) and secondarily by O-demethylation. At least five human uridine diphosphoglucuronosyltransferase (UGT) isozymes catalyze arformoterol glucuronidation in vitro. Two cytochrome P450 isozymes (CYP2D6 and secondarily CYP2C19) catalyze the O-demethylation of arformoterol.

Arformoterol was almost entirely metabolized following oral administration of 35 mcg of radiolabeled arformoterol in eight healthy subjects. Direct conjugation of arformoterol with glucuronic acid was the major metabolic pathway. Most of the drug-related material in plasma and urine was in the form of glucuronide or sulfate conjugates of arformoterol. O-Desmethylation and conjugates of the O-desmethyl metabolite were relatively minor metabolites accounting for less than 17% of the dose recovered in urine and feces.

Elimination

After administration of a single oral dose of radiolabeled arformoterol to eight healthy male subjects, 63% of the total radioactive dose was recovered in urine and 11% in feces within 48 hours. A total of 89% of the total radioactive dose was recovered within 14 days, with 67% in urine and 22% in feces. Approximately 1% of the dose was recovered as unchanged arformoterol in urine over 14 days. Renal clearance was 8.9 L/hr for unchanged arformoterol in these subjects.

In COPD patients given 15 mcg inhaled arformoterol twice a day for 14 days, the mean terminal half-life of arformoterol was 26 hours.

Special Populations:

Gender

A population PK analysis indicated that there was no effect of gender upon the pharmacokinetics of arformoterol.

Race

The influence of race on arformoterol pharmacokinetics was assessed using a population PK analysis and data from healthy subjects. There was no clinically significant impact of race upon the pharmacokinetic profile of arformoterol.

Geriatric

The pharmacokinetic profile of arformoterol in 24 elderly subjects (aged 65 years or older) was compared to a younger cohort of 24 subjects (18-45 years) that were matched for body weight and gender. No significant differences in systemic exposure (AUC and Cmax) were observed when the two groups were compared.

Pediatric

The pharmacokinetics of arformoterol have not been studied in pediatric subjects.

Hepatic Impairment

The pharmacokinetic profile of arformoterol was assessed in 24 subjects with mild, moderate, and severe hepatic impairment. The systemic exposure (Cmax and AUC) to arformoterol increased 1.3 to 2.4-fold in subjects with hepatic impairment compared to 16 demographically matched healthy control subjects. No clear relationship between drug exposure and the severity of hepatic impairment was observed. BROVANA Inhalation Solution should be used cautiously in patients with hepatic impairment.

Renal Impairment

The impact of renal disease upon the pharmacokinetics of arformoterol was studied in 24 subjects with mild, moderate, or severe renal impairment. Systemic exposure (AUC and Cmax) to arformoterol was similar in renally impaired patients compared with demographically matched healthy control subjects.

Drug-Drug Interaction

When paroxetine, a potent inhibitor of CYP2D6, was co-administered with BROVANA Inhalation Solution at steady-state, exposure to either drug was not altered. Dosage adjustments of BROVANA Inhalation Solution are not necessary when the drug is given concomitantly with potent CYP2D6 inhibitors.

Arformoterol did not inhibit CYP1A2, CYP2A6, CYP2C9/10, CYP2C19, CYP2D6, CYP2E1, CYP3A4/5, or CYP4A9/11 enzymes at >1,000-fold higher concentrations than the expected peak plasma concentrations following a therapeutic dose.

12.5 Pharmacogenomics

Arformoterol is eliminated through the action of multiple drug metabolizing enzymes. Direct glucuronidation of arformoterol is mediated by several UGT enzymes and is the primary elimination route. O-Desmethylation is a secondary route catalyzed by the CYP enzymes CYP2D6 and CYP2C19. In otherwise healthy subjects with reduced CYP2D6 and/or UGT1A1 enzyme activity, there was no impact on systemic exposure to arformoterol compared to subjects with normal CYP2D6 and/or UGT1A1 enzyme activities.

13 NONCLINICAL TOXICOLOGY

13.1 Carcinogenesis, Mutagenesis, Impairment of Fertility

Long-term studies were conducted in mice using oral administration and rats using inhalation administration to evaluate the carcinogenic potential of arformoterol.

In a 24-month carcinogenicity study in CD-1 mice, arformoterol caused a dose-related increase in the incidence of uterine and cervical endometrial stromal polyps and stromal cell sarcoma in female mice at oral doses of 1,000 mcg/kg and above (AUC exposure approximately 70 times adult exposure at the MRHDID).

In a 24-month carcinogenicity study in Sprague-Dawley rats, arformoterol caused a statistically significant increase in the incidence of thyroid gland c-cell adenoma and carcinoma in female rats at an inhalation dose of 200 mcg/kg (AUC exposure approximately 130 times adult exposure at the MRHDID). There were no tumor findings with an inhalation dose of 40 mcg/kg (AUC exposure approximately 55 times adult exposure at the MRHDID).

Arformoterol was not mutagenic or clastogenic in the following tests: mutagenicity tests in bacteria, chromosome aberration analyses in mammalian cells, and micronucleus test in mice.

Arformoterol had no effects on fertility and reproductive performance in rats at oral doses up to 10,000 mcg/kg (approximately 3,200 times the MRHDID in adults on a mcg/m^2 basis).

13.2 Animal Toxicology and/or Pharmacology

Animal Pharmacology

In animal studies investigating its cardiovascular effects, arformoterol induced dose-dependent increases in heart rate and decreases in blood pressure consistent with its pharmacology as a beta-adrenergic agonist. In dogs, at systemic exposures higher than anticipated clinically, arformoterol also induced exaggerated pharmacologic effects of a beta-adrenergic agonist on cardiac function as measured by electrocardiogram (sinus tachycardia, atrial premature beats, ventricular escape beats, PVCs).

Studies in laboratory animals (minipigs, rodents, and dogs) have demonstrated the occurrence of arrhythmias and sudden death (with histologic evidence of myocardial necrosis) when beta-agonists and methylxanthines are administered concurrently. The clinical significance of these findings is unknown.

14 CLINICAL STUDIES

14.1 Adult COPD Trials

BROVANA (arformoterol tartrate) Inhalation Solution was studied in two identical, 12-week, double-blind, placebo- and active-controlled, randomized, multi-center, parallel group trials conducted in the United States (Clinical Trial A and Clinical Trial B). A total of 1,456 adult patients (age range: 34 to 89 years; mean age: 63 years; gender: 860 males and 596 females) with COPD who had a mean FEV1 of 1.3 L (42% of predicted) were enrolled in the two clinical trials. The racial/ethnic distribution in these two trials included 1383 Caucasians, 49 Blacks, 10 Asians, and 10 Hispanics, and 4 patients classified as Other. The diagnosis of COPD was based on a prior clinical diagnosis of COPD, a smoking history (greater than 15 pack-years), age (at least 35 years), spirometry results (baseline FEV1 ≤65% of predicted value and >0.70 L, and a FEV1/forced vital capacity (FVC) ratio ≤70%). About 80% of patients in these studies had bronchodilator reversibility, defined as a 10% or greater increase in FEV1 after inhalation of 2 actuations (180 mcg racemic albuterol from a metered dose inhaler). Both trials compared BROVANA Inhalation Solution 15 mcg twice daily (288 patients), 25 mcg twice daily (292 patients), 50 mcg once daily (293 patients) with placebo (293 subjects). Both trials included salmeterol inhalation aerosol, 42 mcg twice daily as an active comparator (290 patients).

In both 12-week trials, BROVANA Inhalation Solution 15 mcg twice daily resulted in a statistically significant change of approximately 11% in mean FEV1 (as measured by percent change from study baseline FEV1 at the end of the dosing interval over the 12 weeks of treatment, the primary efficacy endpoint) compared to placebo. Compared to BROVANA Inhalation Solution 15 mcg twice daily, BROVANA Inhalation Solution 25 mcg twice daily and 50 mcg once daily did not provide sufficient additional benefit on a variety of endpoints, including FEV1, to support the use of higher doses. Plots of the mean change in FEV1 values obtained over the 12 hours after dosing for the BROVANA Inhalation Solution 15 mcg twice daily dose group and for the placebo group are provided in Figures 1 and 2 for Clinical Trial A, below. The plots include mean FEV1 change observed after the first dose and after 12 weeks of treatment. The results from Clinical Trial B were similar.

Figure 1 Mean Change in FEV1 Over Time for Clinical Trial A at Week 0 (Day 1)

Figure 2 Mean Change in FEV1 Over Time for Clinical Trial A at Week 12

BROVANA Inhalation Solution 15 mcg twice daily significantly improved bronchodilation compared to placebo over the 12 hours after dosing (FEV1 AUC0-12h). This improvement was maintained over the 12-week study period.

Following the first dose of BROVANA Inhalation Solution 15 mcg, the median time to onset of bronchodilation, defined by an FEV1 increase of 15%, occurred at 6.7 min. When defined as an increase in FEV1 of 12% and 200 mL, the time to onset of bronchodilation was 20 min after dosing. Peak bronchodilator effect was generally seen within 1-3 hours of dosing.

In both clinical trials, compared to placebo, patients treated with BROVANA Inhalation Solution demonstrated improvements in peak expiratory flow rates, supplemental ipratropium and rescue albuterol use.

16 HOW SUPPLIED/STORAGE AND HANDLING

BROVANA (arformoterol tartrate) Inhalation Solution is supplied in a single strength (15 mcg of arformoterol, equivalent to 22 mcg of arformoterol tartrate) as 2 mL of a sterile solution in low-density polyethylene (LDPE) unit-dose vials overwrapped in foil. BROVANA Inhalation Solution is available in a shelf-carton containing 30 or 60 unit-dose vials.

NDC 27437-060-30: carton of 30 individually pouched unit-dose vials.

NDC 27437-060-60: carton of 60 individually pouched unit-dose vials.

Storage and Handling

Store BROVANA Inhalation Solution in the protective foil pouch under refrigeration at 36°-46°F (2°-8°C). Protect from light and excessive heat. An opened unit-dose vial should be used right away. Discard any unit-dose vial if the solution is not colorless. Unopened foil pouches of BROVANA Inhalation Solution can also be stored at room temperature 68°-77°F (20°-25°C) for up to 6 weeks. If stored at room temperature, discard if not used after 6 weeks or if past the expiration date, whichever is sooner.

17 PATIENT COUNSELING INFORMATION

Advise the patient to read the FDA-approved patient labeling (Patient Information and Instructions for Use) with each new prescription and refill.

The complete text of the Patient Information is reprinted at the end of this document. Patients should be given the following information:

Serious Asthma-Related Events, Acute Exacerbations or Deteriorations

Patients should be informed that long-acting beta2-adrenergic agonists, such as BROVANA Inhalation Solution, when used as monotherapy [without an inhaled corticosteroid], increase risk of serious asthma-related events, including asthma-related death. BROVANA Inhalation Solution is not indicated for the treatment of asthma.

BROVANA Inhalation Solution is not indicated to relieve acute respiratory symptoms and extra doses should not be used for that purpose. Acute symptoms should be treated with an inhaled, short-acting beta2-agonist (the healthcare provider should prescribe the patient with such medication and instruct the patient in how it should be used). Patients should be instructed to seek medical attention if their symptoms worsen despite recommended doses of BROVANA Inhalation Solution, if BROVANA Inhalation Solution treatment becomes less effective, or if they need more inhalations of a short-acting beta2-agonist than usual.

Appropriate Dosing

Patients should not stop using BROVANA Inhalation Solution unless told to do so by a healthcare provider because symptoms may get worse. Patients should not inhale more than one dose at any one time. The daily dosage of BROVANA Inhalation Solution should not exceed one unit-dose vial (15 mcg) by inhalation twice daily (30 mcg total daily dose). Excessive use of sympathomimetics may cause significant cardiovascular effects, and may be fatal.

Concomitant Therapy

Patients who have been taking inhaled, short-acting beta2-agonists (e.g., levalbuterol) on a regular basis should be instructed to discontinue the regular use of these products and use them only for the symptomatic relief of acute symptoms.

BROVANA Inhalation Solution should not be used in conjunction with other inhaled medications containing long-acting beta2-agonists. Patients should be warned not to stop or change the dose of other concomitant COPD therapy without medical advice, even if symptoms improve after initiating treatment with BROVANA Inhalation Solution.

Common Adverse Reactions with Beta2-agonists

Patients should be informed that treatment with beta2-agonists may lead to adverse reactions that include palpitations, chest pain, rapid heart rate, increased or decreased blood pressure, headache, tremor, nervousness, dry mouth, muscle cramps, nausea, dizziness, fatigue, malaise, low blood potassium, high blood sugar, high blood acid, or trouble sleeping [see Adverse Reactions (6.1)].

Instructions for Administration

It is important that patients understand how to use BROVANA Inhalation Solution with a nebulizer appropriately and how it should be used in relation to other medications to treat COPD they are taking [see the accompanying Patient Information]. Patients should be instructed not to mix other medications with BROVANA Inhalation Solution and not to inject or swallow BROVANA Inhalation Solution. Patients should throw the plastic dispensing vials away immediately after use. Due to their small size, the vials pose a danger of choking to young children.

Women should be advised to contact their physician if they become pregnant or if they are nursing.

FDA-Approved Patient Information

See the accompanying Patient Information.

Manufactured for and Distributed by :

Lupin Pharmaceuticals, Inc.

Baltimore, MD 21202

© 2023 Lupin Inc. All rights reserved. BROVANA is a registered trademark of Lupin Inc. and LUPIN is a registered trademark of Lupin Pharmaceuticals, Inc.

To report adverse events, call 1-800-399-2561. RPIN0186

PATIENT INFORMATION
BROVANA® [Brō vă' -nah]
(arformoterol tartrate) Inhalation Solution

What is BROVANA?
• BROVANA is for long-term use and should be taken 2 times each day (morning and evening), to help control the symptoms of chronic obstructive pulmonary disease (COPD) for better breathing.
• COPD is a chronic lung disease that includes chronic bronchitis, emphysema, or both.
• BROVANA is only for use with a nebulizer .
• Long acting beta2 adrenergic agonist (LABA) medicines, such as BROVANA, help the muscles around the airways in your lungs stay relaxed to prevent symptoms, such as wheezing, cough, chest tightness, and shortness of breath.
• BROVANA is not used to treat sudden symptoms of COPD . Always have a short-acting beta2-agonist medicine (rescue inhaler) with you to treat sudden symptoms of COPD. If you do not have a rescue inhaler, contact your healthcare provider to have one prescribed for you.
• BROVANA is not for the treatment of asthma . It is not known if BROVANA is safe and effective in people with asthma.
• BROVANA should not be used in children . It is not known if BROVANA is safe and effective in children

Do not use BROVANA if you:
• are allergic to arformoterol, racemic formoterol, or any of the ingredients in BROVANA. Ask your healthcare provider if you are not sure. See the end of this leaflet for a complete list of ingredients in BROVANA.
• have asthma.

Before you use BROVANA, tell your healthcare provider about all of your medical conditions, including if you:
• have heart problems
• have high blood pressure
• have seizures
• have thyroid problems
• have diabetes
• have liver problems
• are pregnant or plan to become pregnant. It is not known if BROVANA can harm your unborn baby.
• are breastfeeding or plan to breastfeed. It is not known if the arformoterol or any other ingredients in BROVANA passes into your milk and if it can harm your baby. You and your healthcare provider should decide if you will take BROVANA or breastfeed.

Tell your healthcare provider about all the medicines you take including prescription and over-the-counter medicines, vitamins and herbal supplements. BROVANA and certain other medicines may interact with each other. This may cause serious side effects. Know the medicines you take. Keep a list of them to show your healthcare provider and pharmacist each time you get a new medicine.

How should I use BROVANA? Read the step-by-step Instructions for Use for BROVANA at the end of this Patient Information leaflet.
• Use BROVANA exactly as prescribed. Do not use BROVANA more often than prescribed.
• One unit dose vial of BROVANA is 1 dose. The usual dose of BROVANA is 1 unit dose vial, 2 times a day (morning and evening) breathed in through your nebulizer machine. The 2 doses should be taken about 12 hours apart. Do not use more than 2 unit dose vials of BROVANA a day.
• Do not swallow or inject BROVANA.
• BROVANA is for use with a standard jet nebulizer machine connected to an air compressor. Read the complete instructions for use at the end of this Patient Information leaflet before starting BROVANA.
• Do not mix other medicines with BROVANA in your nebulizer machine.
• While you are using BROVANA 2 times each day:
o Do not use other medicines that contain a long-acting beta2-agonist (LABA) for any reason.
o Do not use your short-acting beta2-agonist medicine on a regular basis (four times a day).
• BROVANA does not relieve sudden symptoms of COPD. Always have a rescue inhaler medicine with you to treat sudden symptoms. If you do not have a rescue inhaler medicine, call your healthcare provider to have one prescribed for you.
• Do not stop using BROVANA or other medicines to control or treat your COPD unless told to do so by your healthcare provider because your symptoms might get worse. Your healthcare provider will change your medicines as needed.
Call your healthcare provider or get emergency medical care right away if your breathing problems worsen with BROVANA, you need to use your rescue medicine more often than usual, or your rescue inhaler medicine does not work as well for you at relieving symptoms.

What are the possible side effects of BROVANA? BROVANA can cause serious side effects, including:
• people with asthma who take long-acting beta2-adrenergic agonist (LABA) medicines, such as arformoterol (the medicine in BROVANA), without also using a medicine called an inhaled corticosteroid have an increased risk of serious problems from asthma, including being hospitalized, needing a tube placed in their airway to help them breath, or death.
o Call your healthcare provider if breathing problems worsen over time while using BROVANA. You may need a different treatment.
o Get emergency medical care if:
• your breathing problems worsen quickly.
• you use a rescue inhaler medicine, but it does not relieve your breathing problems.
• COPD symptoms that get worse over time. If your COPD symptoms worsen over time, do not increase your dose of BROVANA, instead call your healthcare provider.
• using too much of a LABA medicine may cause:
o chest pain
o fast and irregular heartbeat
o tremor
o increased blood pressure
o headache
o nervousness
• sudden shortness of breath immediately after use of BROVANA. Sudden shortness of breath may be life threating. If you have sudden breathing problems immediately after inhaling your medicine, stop taking BROVANA and call your healthcare provider or go to the nearest hospital emergency room right away.
• effects on the heart which may include:
o increased blood pressure
o chest pain
o a fast or irregular heartbeat, awareness of a heartbeat
• serious allergic reactions including rash, hives, swelling of the face, mouth, and tongue, and breathing problems. Call your healthcare provider or get emergency medical care if you get any symptoms of a serious allergic reaction.
• Changes in laboratory levels, including high levels of blood sugar (hyperglycemia) and low levels of potassium (hypokalemia).

Common side effects of BROVANA include:
• pain
• sinus congestion
• rash
• chest congestion or bronchitis
• chest or back pain
• leg cramps
• flu-like symptoms
• diarrhea
• trouble breathing
• swelling in your legs

Tell your healthcare provider if you get any side effect that bothers you or that does not go away.
These are not all the possible side effects of BROVANA. Call your doctor for medical advice about side effects. You may report side effects to FDA at 1-800-FDA-1088.

How should I store BROVANA?
• Store BROVANA in a refrigerator between 36° to 46°F (2° to 8°C) in the protective foil pouch. Protect from light and excessive heat. Do not open a sealed pouch until you are ready to use a dose of BROVANA. After opening the pouch, unused unit dose vials should be returned to, and stored in, the pouch. An opened unit dose vial should be used right away.
• BROVANA may also be stored at room temperature between 68º to 77ºF (20º to 25ºC) for up to 6 weeks (42 days). If stored at room temperature, discard BROVANA if it is not used after 6 weeks or if past the expiration date, whichever is sooner. Space is provided on the packaging to record room temperature storage times.
• Do not use BROVANA after the expiration date provided on the foil pouch and unit dose vial.
• BROVANA should be colorless. Throw away (discard) BROVANA if it is not colorless.
• Keep BROVANA and all medicines out of the reach of children.

General information about the safe and effective use of BROVANA. Medicines are sometimes prescribed for purposes not mentioned in this Patient Information leaflet. Do not use BROVANA for a condition for which it was not prescribed. Do not give BROVANA to other people, even if they have the same symptoms that you may have. It may harm them. You can ask your pharmacist or healthcare provider for information about BROVANA that was written for health professionals.

What are the ingredients in BROVANA? Active ingredient: arformoterol Inactive ingredients: citric acid and sodium citrate

Manufactured for and Distributed by :
Lupin Pharmaceuticals, Inc.
Baltimore, MD 21202
© 2023 Lupin Inc. All rights reserved.
BROVANA is a registered trademark of Lupin Inc. and LUPIN is a registered trademark of Lupin Pharmaceuticals, Inc.
This Patient Information has been approved by the Food and Drug Administration.
Revised: 12/2023

Instructions for Using BROVANA (arformoterol tartrate) Inhalation Solution

BROVANA is used only in a standard jet nebulizer machine connected to an air compressor. Make sure you know how to use your nebulizer machine before you use it to breathe in BROVANA or other medicines.

Do not mix BROVANA with other medicines in your nebulizer machine.

BROVANA comes sealed in a foil pouch. Do not open a sealed pouch until you are ready to use a dose of BROVANA. After opening the pouch, unused unit dose vials should be returned to, and stored in, the pouch. An opened unit dose vial should be used right away.

1. Open the foil pouch by tearing on the rough edge along the seam of the pouch. Remove a unit dose vial of BROVANA.

2. Carefully twist open the top of the unit dose vial and use it right away (Figure 1).

Figure 1

3. Squeeze all of the medicine from the unit dose vial into the nebulizer medicine cup (reservoir) (Figure 2).

Figure 2

4. Connect the nebulizer reservoir to the mouthpiece (Figure 3) or face mask (Figure 4).

Figure 3

Figure 4

5. Connect the nebulizer to the compressor (Figure 5).

Figure 5

6. Sit in a comfortable, upright position. Place the mouthpiece in your mouth (Figure 6) (or put on the face mask) and turn on the compressor.

Figure 6

7. Breathe as calmly, deeply, and evenly as possible until no more mist is formed in the nebulizer reservoir. It takes about 5 to 10 minutes for each treatment.

8. Clean the nebulizer (see manufacturer's instructions).

Rx Only

This Instructions for Use has been approved by the Food and Drug Administration.

Manufactured for and Distributed by :

Lupin Pharmaceuticals, Inc.

Baltimore, MD 21202

© 2023 Lupin Inc. All rights reserved.

BROVANA is a registered trademark of Lupin Inc. and LUPIN is a registered trademark of Lupin Pharmaceuticals, Inc.

12/2023 RPIN0186

PACKAGE LABEL – PRINCIPAL DISPLAY PANEL – 60 VIAL CARTON

NDC 27437-060-60

60x 2mL Sterile Unit-Dose Vials

KEEP REFRIGERATED OR STORE AT ROOM TEMPERATURE

FOR UP TO 6 WEEKS.

Brovana®

(arformoterol tartrate)

Inhalation Solution

15 mcg* / 2 mL

* Potency expressed as arformoterol

For Oral Inhalation Only.

Rx Only

PACKAGE LABEL – PRINCIPAL DISPLAY PANEL – 30 VIAL CARTON

NDC 27437-060-30

30x 2mL Sterile Unit-Dose Vials

KEEP REFRIGERATED OR STORE AT ROOM TEMPERATURE

FOR UP TO 6 WEEKS.

Brovana®

(arformoterol tartrate)

Inhalation Solution

15 mcg* / 2 mL

* Potency expressed as arformoterol

For Oral Inhalation Only.

Rx Only

PACKAGE LABEL – PRINCIPAL DISPLAY PANEL – Single VIAL POUCH

NDC 27437-060-01

One 2 mL Sterile Unit-Dose Vial.

Brovana®

(arformoterol tartrate)

Inhalation Solution

15 mcg* / 2 mL

* Potency expressed as arformoterol

Open Foil Pouch Just Prior to Administration

Each 2 mL unit-dose vial contains 15mcg of arformoterol (equivalent to 22 mcg arformoterol tartrate) in a sterile, isotonic saline solution, pH- adjusted to 5.0 with citric acid and sodium citrate.

Keep out of reach of children. Rx Only.

Protect from light and excessive heat. Store unopened pouched unit-dose vials in a refrigerator (36ºF-46ºF, 2ºC-8ºC). Unopened pouched unit-dose vials can also be stored at room temperature (68ºF-77ºF, 20ºC-25ºC) for up to 6 weeks. Do not use past the expiration date or after 6 weeks storage at room temperature, whichever is sooner. Discard if solution is not colorless. Use only as directed by your physician. Do not exceed recommended dosage.